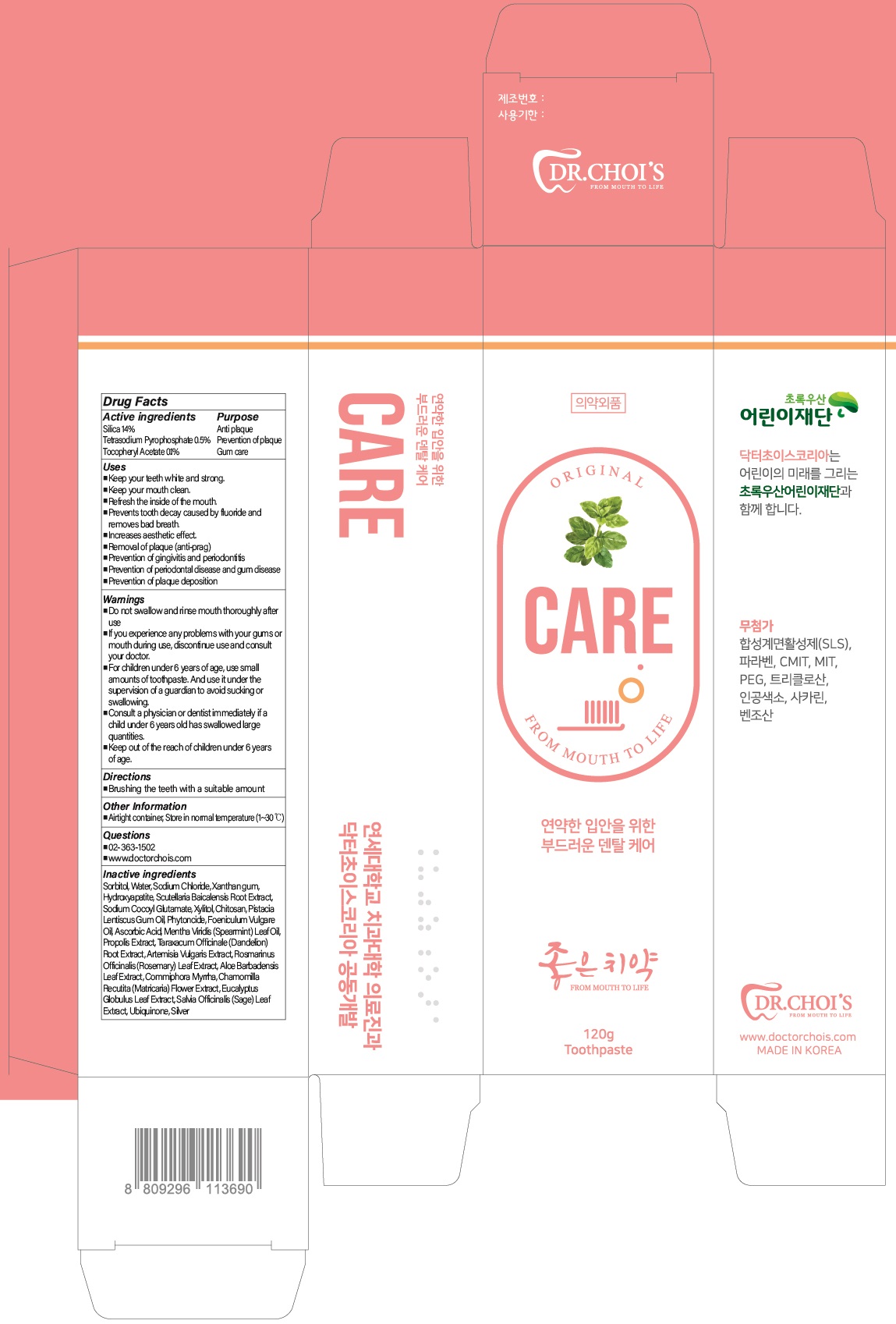 DRUG LABEL: DR.CHOIS TOOTHPASTE CARE
NDC: 73666-0510 | Form: PASTE, DENTIFRICE
Manufacturer: Doctor Choi`s Korea Co., LTD.
Category: otc | Type: HUMAN OTC DRUG LABEL
Date: 20220920

ACTIVE INGREDIENTS: SILICON DIOXIDE 14.0 g/100 g; SODIUM PYROPHOSPHATE 0.5 g/100 g; .ALPHA.-TOCOPHEROL ACETATE 0.1 g/100 g
INACTIVE INGREDIENTS: Sorbitol; Water; Sodium Chloride

ACTIVE INGREDIENTS

Silica 14%
Tetrasodium Pyrophosphate 0.5%
Tocopheryl Acetate 0.1%

PURPOSE

Anti plaque
Prevention of plaque
Gum care

Uses

■ Keep your teeth white and strong.
■ Keep your mouth clean.
■ Refresh the inside of the mouth.
■ Prevents tooth decay caused by fluoride and removes bad breath.
■ Increases aesthetic effect.
■ Removal of plaque (anti-prag)
■ Prevention of gingivitis and periodontitis
■ Prevention of periodontal disease and gum disease
■ Prevention of plaque deposition

WARNINGS

■ Do not swallow and rinse mouth thoroughly after use
■ If you experience any problems with your gums or mouth during use,
discontinue use and consult your doctor.
■ For children under 6 years of age, use small amounts of toothpaste. And use it
under the supervision of a guardian to avoid sucking or swallowing.
■ Consult a physician or dentist immediately if a child under 6 years old has
swallowed large quantities.
■ Keep out of the reach of children under 6 years of age.

KEEP OUT OF REACH OF CHILDREN

■ Keep out of the reach of children under 6 years of age.

Directions

■ Brushing the teeth with a suitable amount

Other Information

■ Airtight container, Store in normal temperature (1~30℃)

Questions

■ 02-363-1502
■ www.doctorchois.com

INACTIVE INGREDIENTS

Sorbitol, Water, Sodium Chloride, Xanthan gum, Hydroxyapatite, Scutellaria Baicalensis Root Extract, Sodium Cocoyl Glutamate, Xylitol, Chitosan, Pistacia Lentiscus Gum Oil, Phytoncide, Foeniculum Vulgare Oil, Ascorbic Acid, Mentha Viridis (Spearmint) Leaf Oil, Propolis Extract, Taraxacum Officinale (Dandelion)Root Extract, Artemisia Vulgaris Extract, Rosmarinus Officinalis (Rosemary) Leaf Extract, Aloe Barbadensis Leaf Extract, Commiphora Myrrha, Chamomilla Recutita (Matricaria) Flower Extract, Eucalyptus Globulus Leaf Extract, Salvia Officinalis (Sage) Leaf Extract, Ubiquinone, Silver